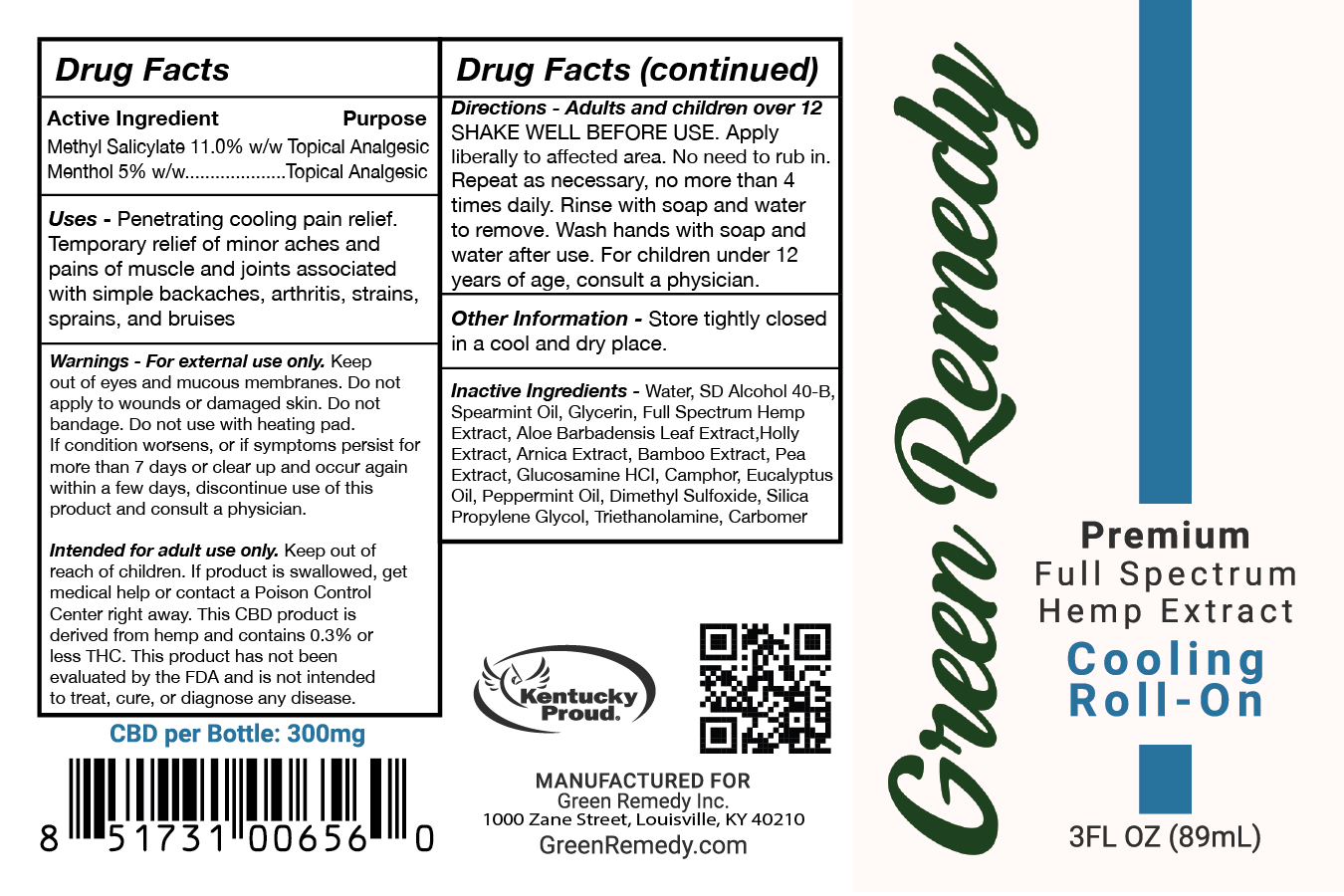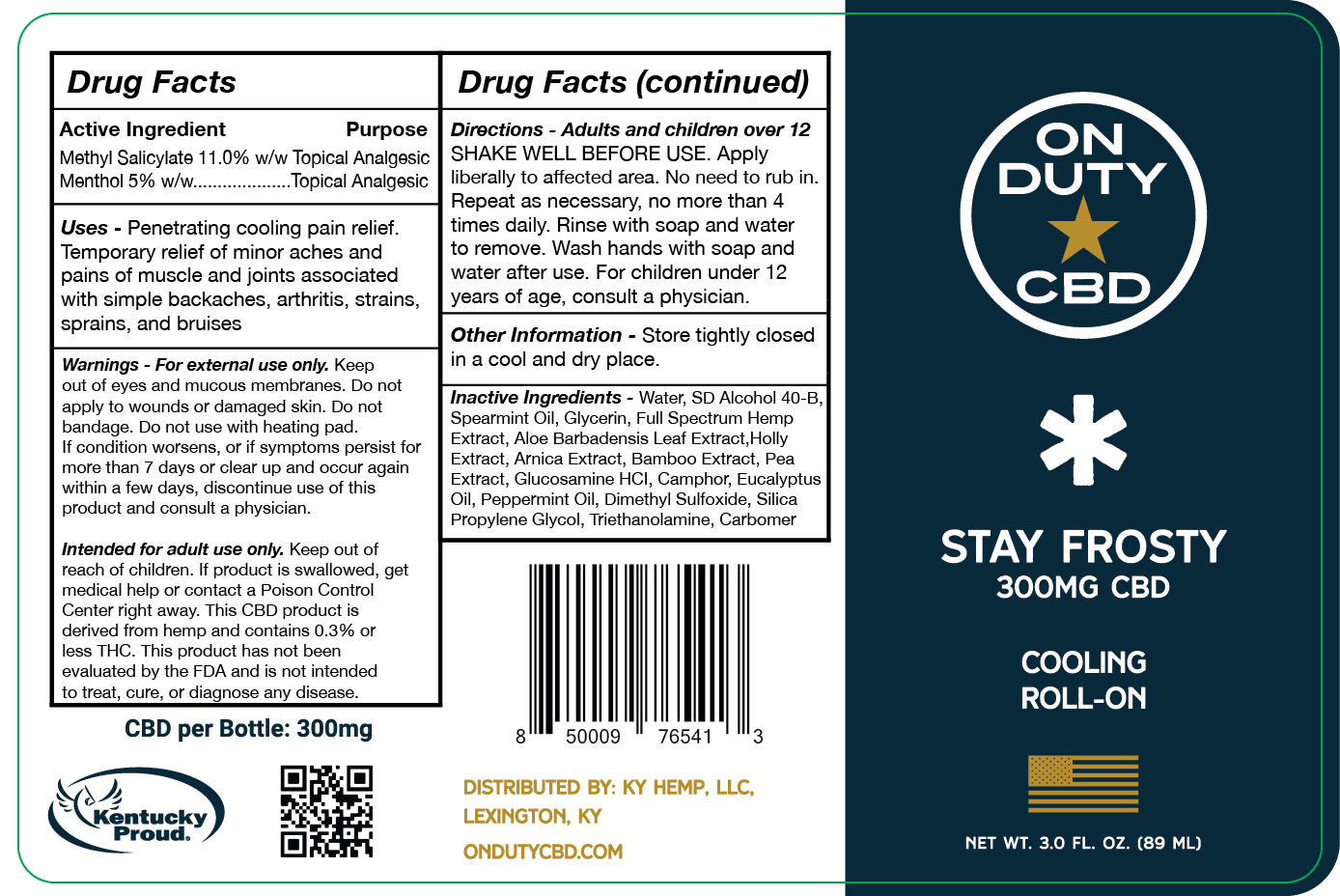 DRUG LABEL: GREEN REMEDY COOLING ROLL ON
NDC: 78461-0002 | Form: GEL
Manufacturer: EXCLAVE HOLDINGS INC.
Category: otc | Type: HUMAN OTC DRUG LABEL
Date: 20210222

ACTIVE INGREDIENTS: METHYL SALICYLATE 1 g/1 g; MENTHOL, UNSPECIFIED FORM 1 g/1 g
INACTIVE INGREDIENTS: SPEARMINT OIL; GLYCERIN; ILEX AQUIFOLIUM LEAF; BAMBUSA VULGARIS TOP; GLUCOSAMINE HYDROCHLORIDE; CAMPHOR (SYNTHETIC); EUCALYPTUS OIL; CARBOMER INTERPOLYMER TYPE B (ALLYL PENTAERYTHRITOL CROSSLINKED); PEA; TROLAMINE; ALCOHOL; WATER; ARNICA MONTANA FLOWER; PEPPERMINT OIL; DIMETHYL SULFOXIDE; PROPYLENE GLYCOL; ALOE VERA LEAF

Green Remedy 300mg Cooling Roll On

INACTIVE INGREDIENT

Water

SD Alcohol 40-B

Spearmint Oil

Glycerin

Full Spectrum Hemp Extract

Aloe Barbadensis Leaf Extract

Holly Extract

Arnica Extract

Bamboo Extract

Pea Extract

Glucosamine HCI

Camphor

Eucalyptus Oil

Peppermint Oil

Dimethyl Sulfoxide

Silica Propylene Glycol

Triethanolamine

Carbomer

INDICATIONS AND USAGE

Temporary relief of minor aches and pains of muscle and joints associated with simple backaches, arthritis, strains, sprains, and bruises.

Shake well before use. Apply liberally to affected area. No need to rub in. Repeat if necessary, no more than 4 times daily. Rinse with soap and water to remove. Wash hands with soap and water after use. For children under 12 years of age, consult a physician.

KEEP OUT OF REACH OF CHILDREN

Intended for adult use only. Keep out of reach of children. If product is swallowed, get medical help or contact a Poison Control Center right away.

PURPOSE

Penetrating cooling relief. Temporary relief of minor aches and pains of muscle and joints associated with simple backaches, arthritis, strains, sprains, and bruises.

ACTIVE INGREDIENT

Methyl Salicylate

Menthol

DOSAGE AND ADMINISTRATION

Apply liberally to affected area. No need to rub in. Repeat as necessary, no more than 4 times daily.

WARNINGS

For external use only. Keep out of eyes and mucous membranes. Do not apply to wounds or damaged skin. Do not bandage. Do not use with heating pad. If condition worsens, or if symptoms persist for more than 7 days or clear up and occur again within a few days, discontinue use of this product and consult a physician.

PACKAGE LABEL

89mg NDC: 78461-0002-1

89mg NDC: 78461-0002-1